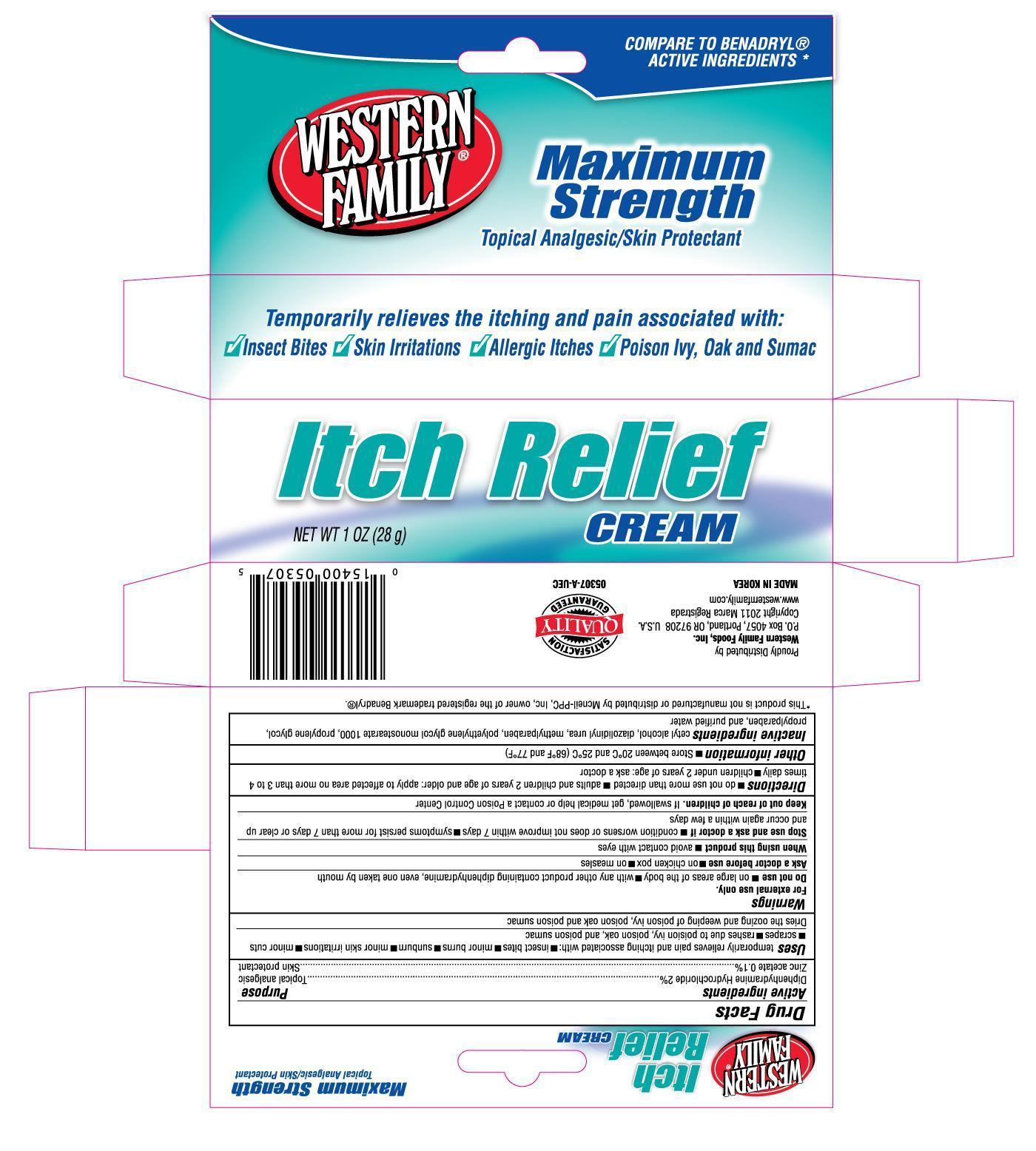 DRUG LABEL: Western Family Itch Relief
                
NDC: 55312-053 | Form: CREAM
Manufacturer: Western Family Food, Inc.
Category: otc | Type: HUMAN OTC DRUG LABEL
Date: 20130430

ACTIVE INGREDIENTS: DIPHENHYDRAMINE HYDROCHLORIDE 2 g/100 g; ZINC ACETATE 0.1 g/100 g
INACTIVE INGREDIENTS: CETYL ALCOHOL; DIAZOLIDINYL UREA; METHYLPARABEN; PROPYLENE GLYCOL; PROPYLPARABEN; WATER

Drug Facts

Active ingredients Purpose

Diphenhydramine Hydrochloride 2%..............................................................Topical analgesic

Zinc acetate 0.1%..........................................................................................Skin protectant

PURPOSE

Uses temporarily relieves pain and itching associated with:

- insect bites
- minor burns
- sunburn
- minor skin irritations
- minor cuts
- scrapes
- rashes due to poison ivy, poison oak and poison sumac
- Dries the oozing and weeping of poison ivy, poison oak, and poison sumac

Warnings For external use only.

Do not use

- on large areas of the body
- with any other product containing diphenhydramine, even one taken by mouth

Ask a doctor before use

- on chicken pox
- on measles

When using this product

- avoid contact with eyes

Stop use and ask a doctor if

- condition worsens or does not improve within 7 days
- symptoms persist for more than 7 days or clear up and occur again within a few days

Keep out of reach of children. If swallowed, get medical help or contact a Poison Control Center.

Directions

- do not use more than directed
- adults and children 2 years of age and older: apply to affected area no more than 3 to 4 times daily
- children under 2 years of age: ask a doctor

Other information

- store between 20°C and 25°C (68°F and 77°F)

INACTIVE INGREDIENT

Inactive ingredients cetyl alcohol, diazolidinyl urea, methylparaben, polyethylene glycol monostearate 1000, propylene glycol, propylparaben, and purified water

DOSAGE AND ADMINISTRATION

Proudly Distributed by:

Western Family Foods, Inc.

P.O. Box 4057

Portland, OR 97208 U.S.A.

Made in Korea